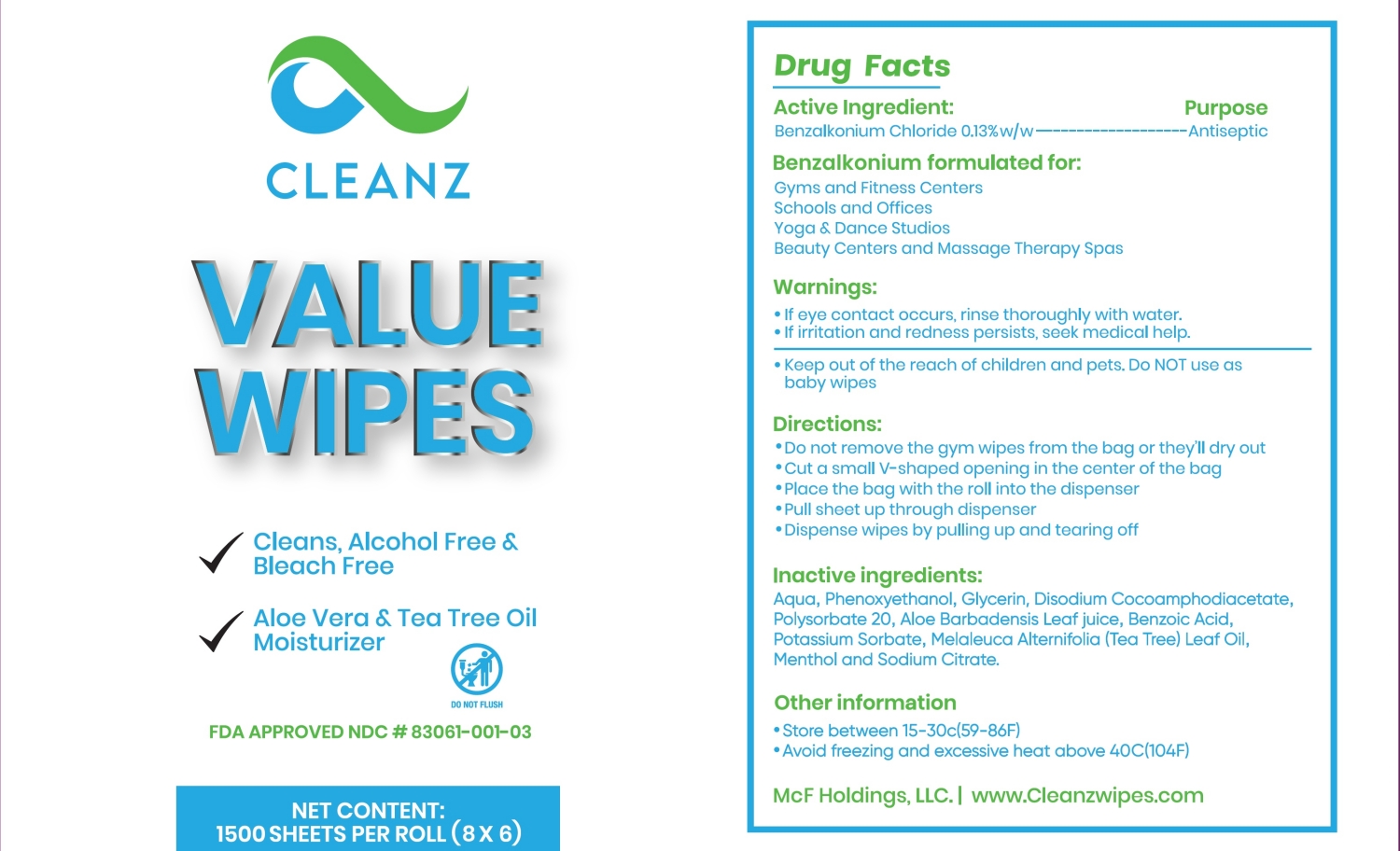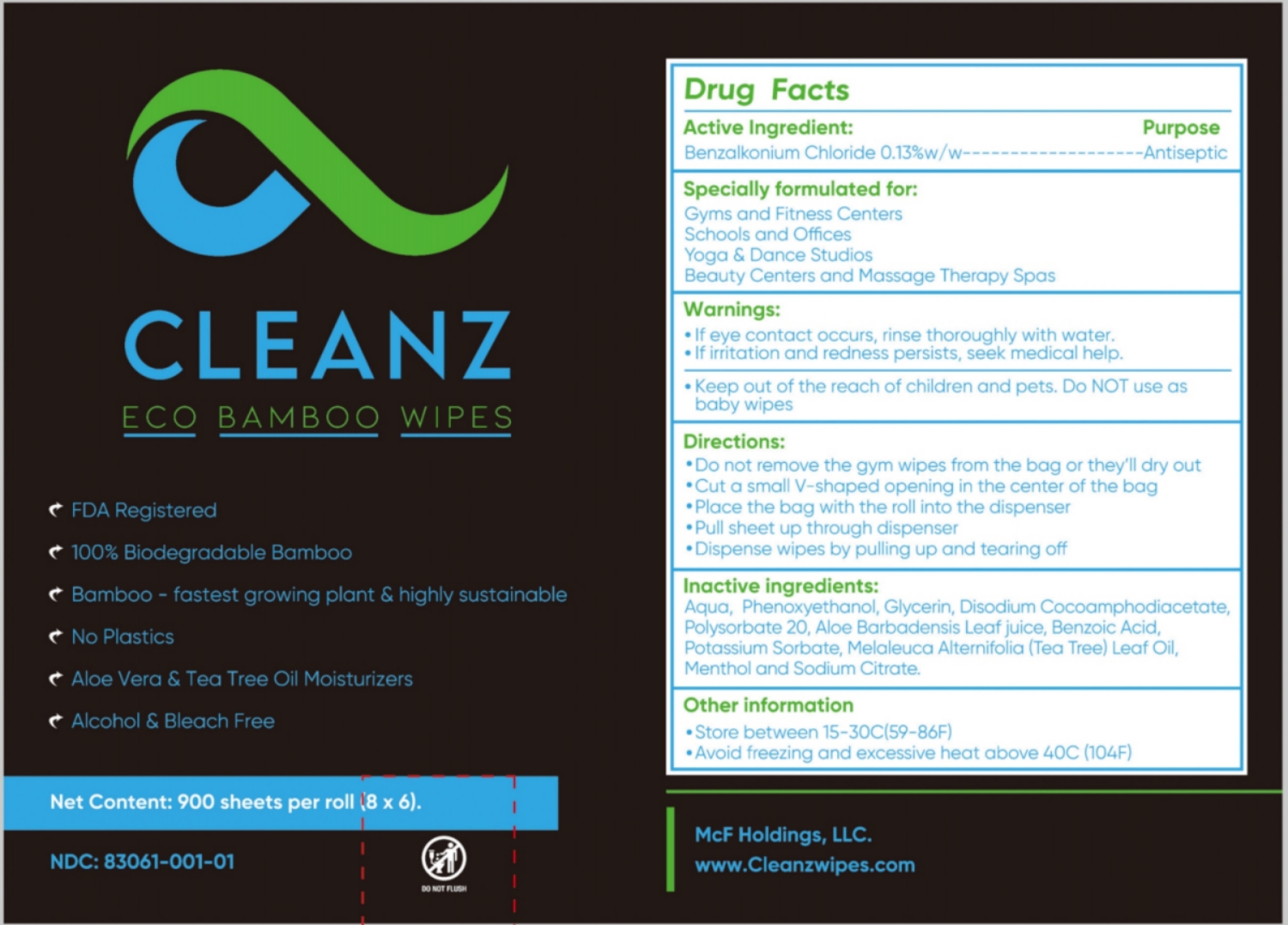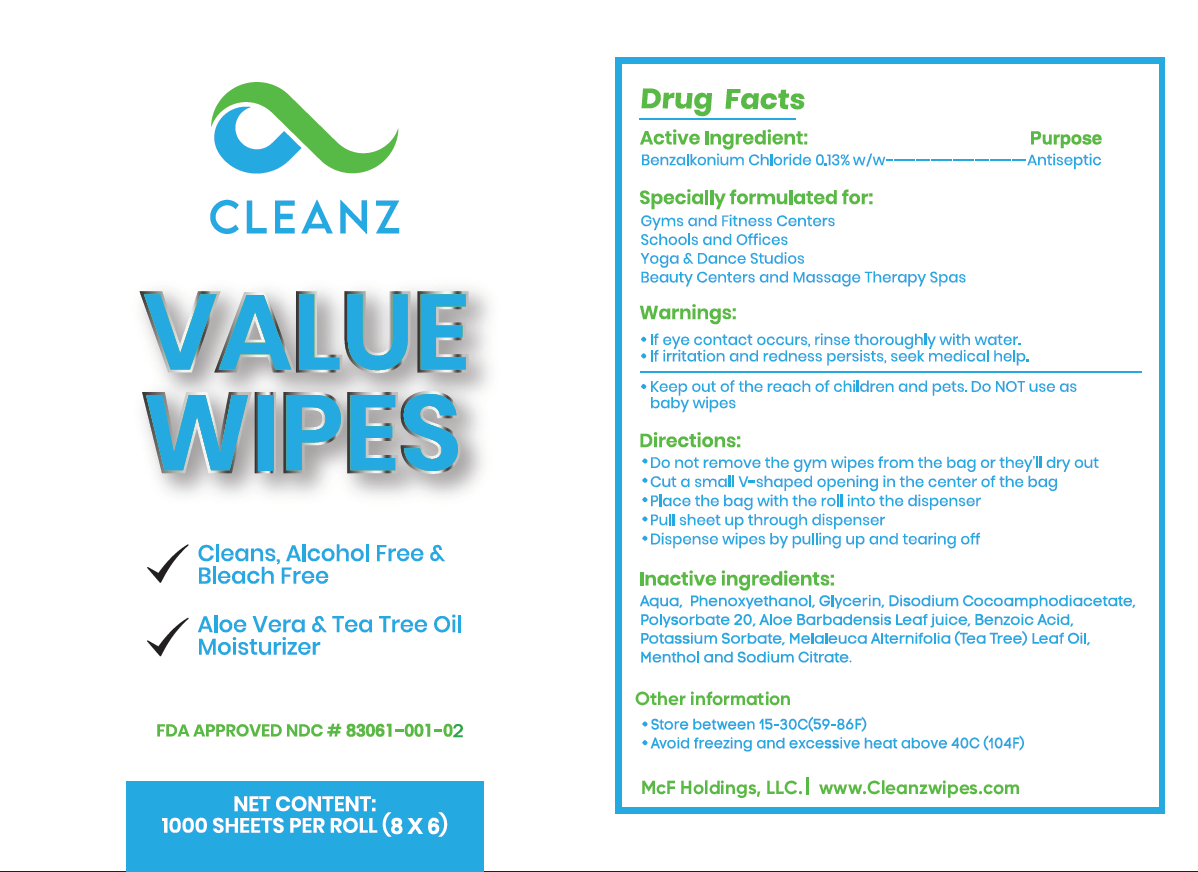 DRUG LABEL: CLEANZ ECO BAMBOO WIPES
NDC: 83061-001 | Form: CLOTH
Manufacturer: McF Holdings LLC
Category: otc | Type: HUMAN OTC DRUG LABEL
Date: 20251224

ACTIVE INGREDIENTS: BENZALKONIUM CHLORIDE 0.13 g/100 g
INACTIVE INGREDIENTS: AQUA; POLYSORBATE 20; DISODIUM COCOAMPHODIACETATE; PHENOXYETHANOL; BENZOIC ACID; ALOE BARBADENSIS LEAF JUICE; MENTHOL; SODIUM CITRATE; GLYCERIN; POTASSIUM SORBATE; MELALEUCA ALTERNIFOLIA (TEA TREE) LEAF OIL

83061-001 CLEANZ ECO BAMBOO WIPES

Active Ingredient

Benzalkonium Chloride 0.13%w/w

Purpose

Antiseptic

INDICATIONS AND USAGE

Specially formulated for:

Gyms and Fitness Centers

Schools and Offices

Yoga & Dance Studios

Beauty Centers and Massage Therapy Spas

Warnings

·If eye contact occurs, rinse thoroughly with water.

·If irritation and redness persists, seek medical help.

·Keep out of the reach of children and pets. Do NOT use as baby wipes.

KEEP OUT OF REACH OF CHILDREN

Keep out of the reach of children and pets. Do NOT use as baby wipes

Directions:

·Do not remove the gym wipes from the bag or they'll dry out

·Cut a small V-shaped opening in the center of the bag

·Place the bag with the roll into the dispenser

·Pull sheet up through dispenser

·Dispense wipes by pulling up and tearing off

Inactive ingredients:

Aqua, Phenoxyethanol, Glycerin, Disodium Cocoamphodiacetate, Polysorbate 20, Aloe Barbadensis Leaf Juice, Benzoic Acid, Potassium Sorbate, Melaleuca Alternifolia (Tea Tree) Leaf Oil, Menthol and Sodium Citrate.

Other information

·Store between 15-30C(59-86F)
·Avoid freezing and excessive heat above 40C (104F)

PACKAGE LABEL

900 sheets per roll (8 × 6)
NDC: 83061-001-01

PACKAGE LABEL

NDC: 83061-001-02

PACKAGE LABEL

1500 sheets per roll (8 × 6)
NDC: 83061-001-03